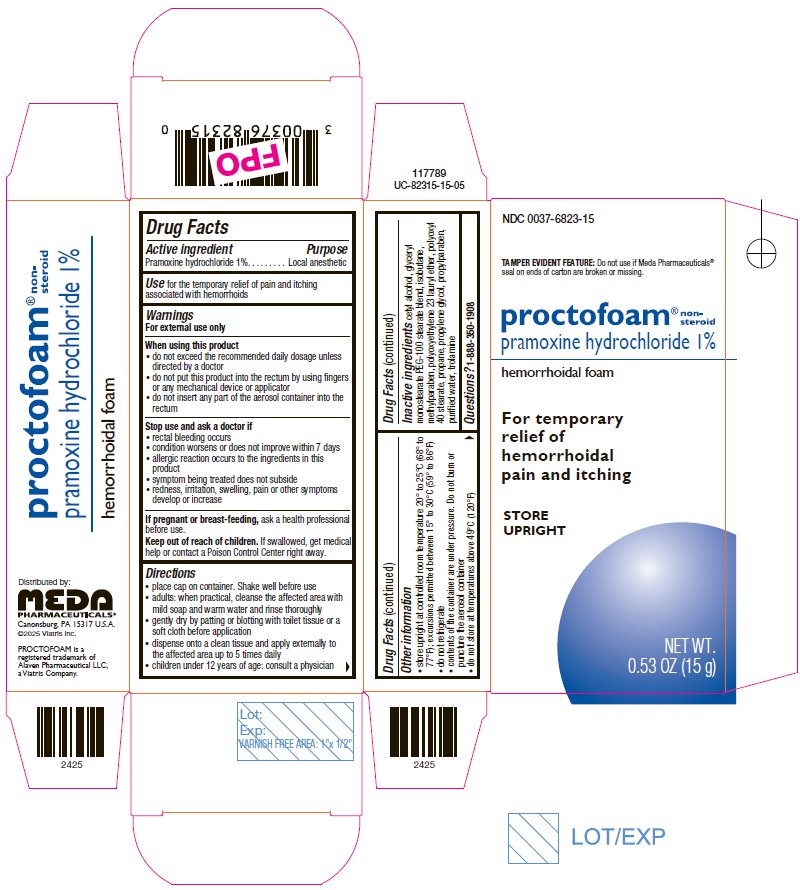 DRUG LABEL: PROCTOFOAM
NDC: 0037-6823 | Form: AEROSOL, FOAM
Manufacturer: Viatris Specialty LLC
Category: otc | Type: HUMAN OTC DRUG LABEL
Date: 20250815

ACTIVE INGREDIENTS: PRAMOXINE HYDROCHLORIDE 150 mg/15 g
INACTIVE INGREDIENTS: CETYL ALCOHOL; GLYCERYL MONOSTEARATE; PEG-100 STEARATE; METHYLPARABEN; LAURETH-23; POLYOXYL 40 STEARATE; PROPYLENE GLYCOL; PROPYLPARABEN; WATER; TROLAMINE; ISOBUTANE; PROPANE

Drug Facts

Active ingredient

Pramoxine hydrochloride 1%

Purpose

Local anesthetic

Use

for the temporary relief of pain and itching associated with hemorrhoids

Warnings

For external use only

When using this product

- do not exceed the recommended daily dosage unless directed by a doctor
- do not put this product into the rectum by using fingers or any mechanical device or applicator
- do not insert any part of the aerosol container into the rectum

Stop use and ask a doctor if

- rectal bleeding occurs
- condition worsens or does not improve within 7 days
- allergic reaction occurs to the ingredients in this product
- symptom being treated does not subside
- redness, irritation, swelling, pain or other symptoms develop or increase

If pregnant or breast-feeding,

ask a health professional before use.

Keep out of reach of children.

If swallowed, get medical help or contact a Poison Control Center right away.

Directions

- place cap on container. Shake well before use
- adults: when practical, cleanse the affected area with mild soap and warm water and rinse thoroughly
- gently dry by patting or blotting with toilet tissue or a soft cloth before application
- dispense onto a clean tissue and apply externally to the affected area up to 5 times daily
- children under 12 years of age: consult a physician

Other information

- store upright at controlled room temperature 20° to 25°C (68° to 77°F); excursions permitted between 15° to 30°C (59° to 86°F)
- do not refrigerate
- contents of the container are under pressure. Do not burn or puncture the aerosol container
- do not store at temperatures above 49°C (120°F)

Inactive ingredients

cetyl alcohol, glyceryl monostearate PEG-100 stearate blend, isobutane, methylparaben, polyoxyethylene 23 lauryl ether, polyoxyl 40 stearate, propane, propylene glycol, propylparaben, purified water, trolamine

Questions?

1-888-350-1908

Distributed by:
Meda Pharmaceuticals Inc.
Canonsburg, PA 15317 U.S.A.

© 2025 Viatris Inc.

PROCTOFOAM is a registered trademark of Alaven Pharmaceutical LLC, a Viatris Company..

Principal Display Panel – 1%

NDC 0037-6823-15

TAMPER EVIDENT FEATURE: Do not use if Meda Pharmaceuticals® seal on ends of carton are broken or missing.

proctofoam® non-steroid
pramoxine hydrochloride 1%
hemorrhoidal foam

For temporary
relief of
hemorrhoidal
pain and itching

STORE
UPRIGHT

NET WT.
0.53 OZ (15 g)

Drug Facts

Active ingredient Purpose
Pramoxine hydrochloride 1%. . . . . . . . Local anesthetic

Use for the temporary relief of pain and itching
associated with hemorrhoids

Warnings
For external use only

When using this product

- do not exceed the recommended daily dosage unless directed by a doctor
- do not put this product into the rectum by using fingers
- or any mechanical device or applicator
- do not insert any part of the aerosol container into the rectum

Stop use and ask a doctor if

- rectal bleeding occurs
- condition worsens or does not improve within 7 days
- allergic reaction occurs to the ingredients in this product
- symptom being treated does not subside
- redness, irritation, swelling, pain or other symptoms develop or increase

If pregnant or breast-feeding, ask a health professional before use.

Keep out of reach of children. If swallowed, get medical help or contact a Poison Control Center right away.

Directions

- place cap on container. Shake well before use
- adults: when practical, cleanse the affected area with mild soap and warm water and rinse thoroughly
- gently dry by patting or blotting with toilet tissue or a soft cloth before application
- dispense onto a clean tissue and apply externally to the affected area up to 5 times daily
- children under 12 years of age: consult a physician

Drug Facts (continued)

Other information

- store upright at controlled room temperature 20° to 25°C (68° to 77°F); excursions permitted between 15° to 30°C (59° to 86°F)
- do not refrigerate
- contents of the container are under pressure. Do not burn or puncture the aerosol container
- do not store at temperatures above 49°C (120°F)

Drug Facts (continued)

Inactive ingredients cetyl alcohol, glyceryl monostearate PEG-100 stearate blend, isobutane, methylparaben, polyoxyethylene 23 lauryl ether, polyoxyl 40 stearate, propane, propylene glycol, propylparaben, purified water, trolamine

Questions? 1-888-350-1908

Distributed by:
MEDA PHARMACEUTICALS®
Canonsburg, PA 15317 U.S.A.
©2025 Viatris Inc.

PROCTOFOAM is a
registered trademark of
Alaven Pharmaceutical LLC,
a Viatris Company.

117789
UC-82315-15-05